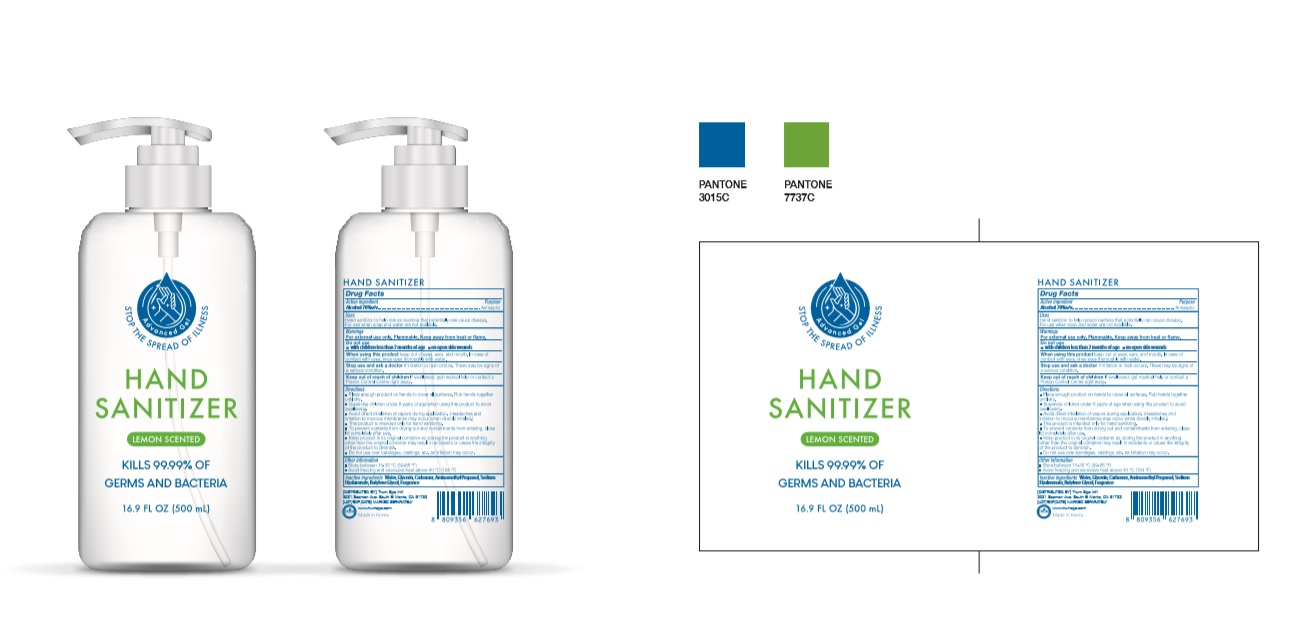 DRUG LABEL: TRUM HAND SANITIZER
NDC: 74339-5557 | Form: GEL
Manufacturer: PL COSMETIC
Category: otc | Type: HUMAN OTC DRUG LABEL
Date: 20200413

ACTIVE INGREDIENTS: ALCOHOL 350 mL/500 mL
INACTIVE INGREDIENTS: GLYCERIN; CARBOMER HOMOPOLYMER, UNSPECIFIED TYPE; WATER; BUTYLENE GLYCOL; HYALURONATE SODIUM; AMINOMETHYLPROPANOL

TRUM HAND SANITIZER 500 ml : 74339-5557